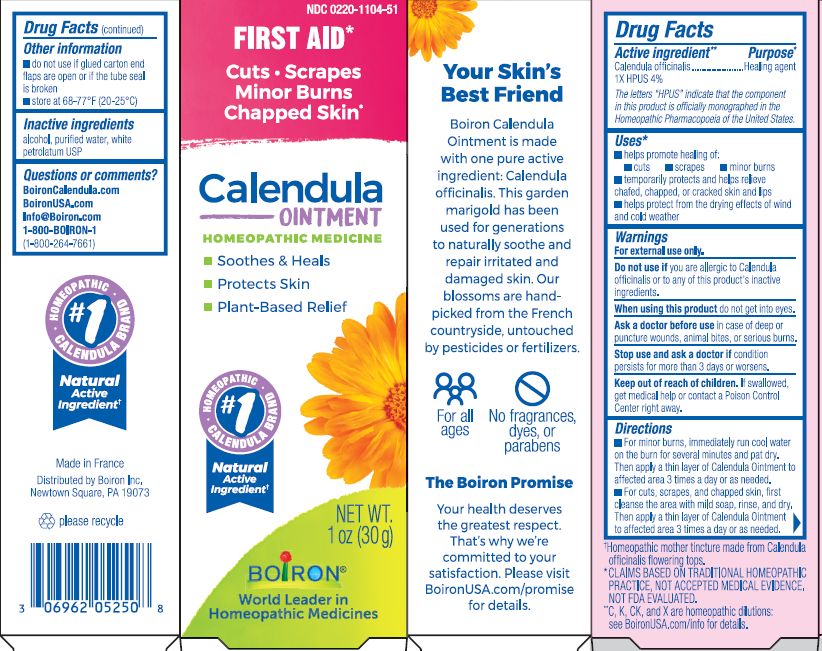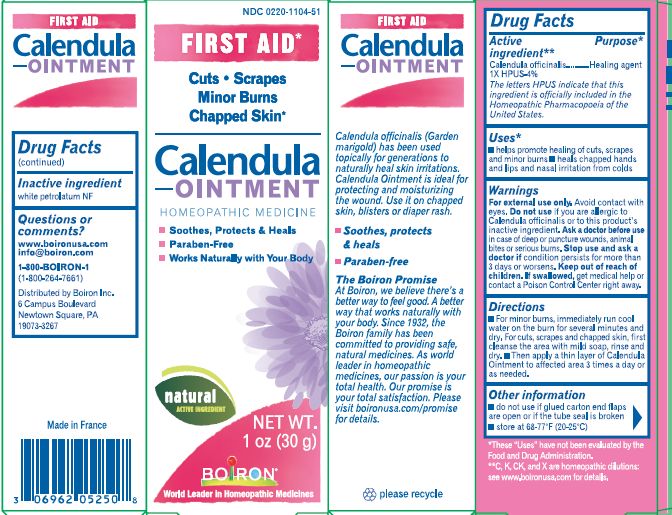 DRUG LABEL: Calendula
NDC: 0220-1104 | Form: OINTMENT
Manufacturer: Laboratoires Boiron
Category: homeopathic | Type: HUMAN OTC DRUG LABEL
Date: 20230206

ACTIVE INGREDIENTS: CALENDULA OFFICINALIS FLOWERING TOP 1 [hp_X]/1 g
INACTIVE INGREDIENTS: WATER; ALCOHOL; PETROLATUM

Calendula ointment

ACTIVE INGREDIENT

Calendula officinalis 1X HPUS 4%

The letters "HPUS" indicate that the components in this product are officially monographed in the Homeopathic Pharmacopoeia of the United States.

PURPOSE

Calendual officianlis 1X HPUS 4% .... Healing agent

INDICATIONS AND USAGE

helps promote healing of: cuts, scrapes, minor burns, temporarily protects and helps relieve chafed, chapped, or cracked skin and lips, helps protect from the drying effects of wind and cold weather

Do not use if glued carton end flaps are open or if the tube seal is broken.

Do not use if you are allergic to Calendula officinalis or to any of this product's inactive ingredients

DOSAGE AND ADMINISTRATION

For minor burns, immediately run cool water on the burn for several minutes and pat dry. Then apply a thin layer of Calendula Ointment to affected area 3 times a day or as needed.

For cuts, scrapes, and chapped skin, first cleanse the area with mild soap, rinse and dry. Then apply a thin layer of Calendula Ointment to affected area 3 times a day or as needed.

INACTIVE INGREDIENT

alcohol, purified water, white petrolatum USP

HOW SUPPLIED

Tube 1 OZ (30 G)

STORAGE AND HANDLING

Store at 68-77O F (20-25O C)

Questions, Comments?

BoironCalendula.com

BoironUSA.com

Info@boironusa.com

1-800-BOIRON-1 (1-800-264-7661)
Distributed by Boiron Inc.
Newtown Square, PA 19073-3267

ASK DOCTOR

Consult a doctor in case of deep or puncture wounds, animal bites or serious burns.

Stop use and ask doctor if condition persists for more than 3 days or worsens.

Keep out of reach of children. In case of accidental overdose, get medical help or contact a Poison Control Center right away.

When using this product do not get into eyes

DRUG INTERACTIONS

Keep wounds moisturized - Paraben-free - Works naturally with your body

WARNINGS

For external use only

†Homeopathic mother tincture made from Calendula officinalis flowering tops.

*CLAIMS BASED ON TRADITIONAL HOMEOPATHIC PRACTICE, NOT ACCEPTED MEDICAL EVIDENCE. NOT FDA EVALUATED.
*C,K,CK, and X are homeopathic dilutions: see BoironUSA.com/info for details.

Soothes & Heals

Protects Skin

Plant-Based Relief

First Aid*

Cuts, Scrapes, Minor Burns, Chapped Skin*